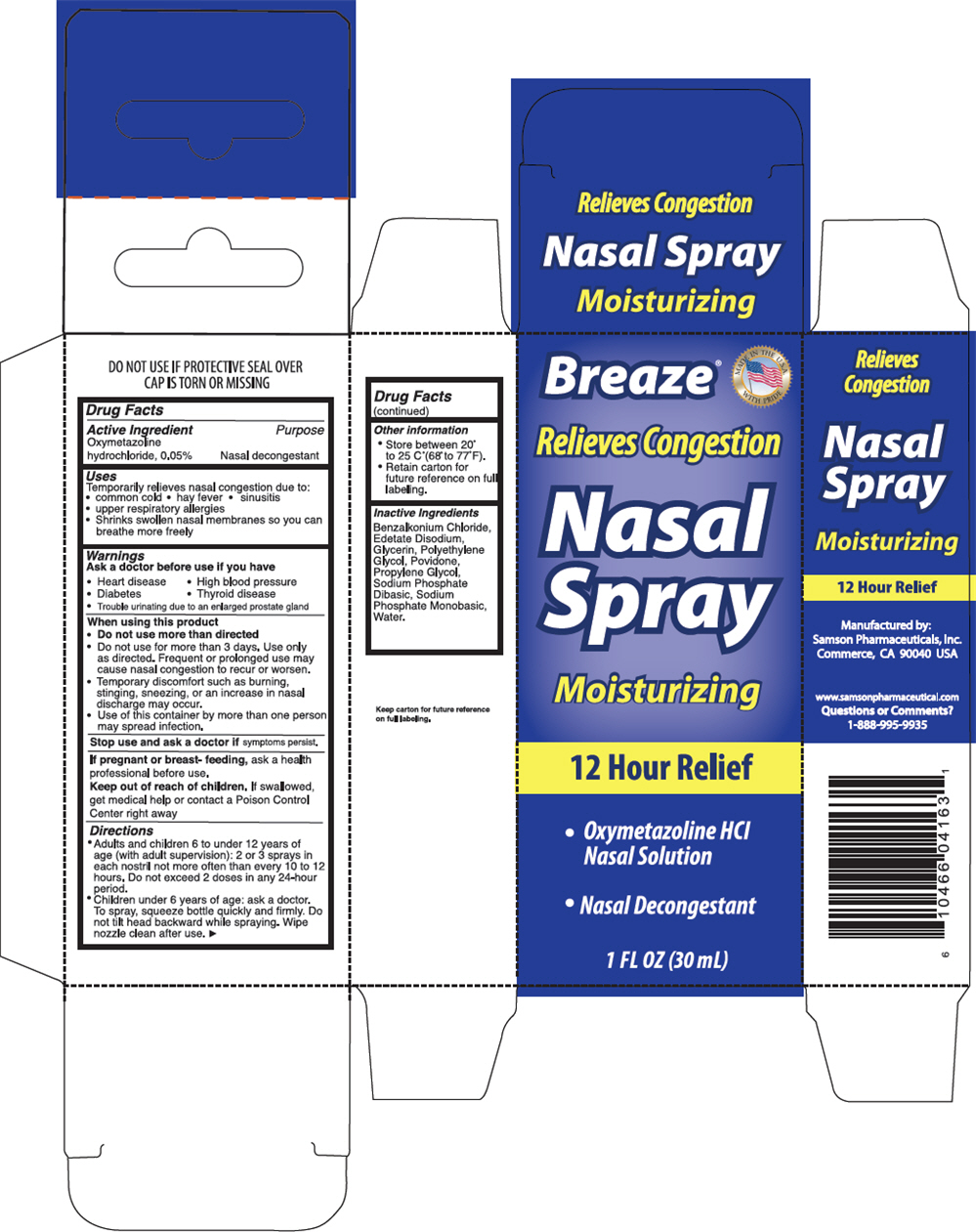 DRUG LABEL: Breaze 
NDC: 20146-4000 | Form: SPRAY
Manufacturer: Samson Pharmaceuticals, Inc.
Category: otc | Type: HUMAN OTC DRUG LABEL
Date: 20221129

ACTIVE INGREDIENTS: Oxymetazoline hydrochloride 0.5 mg/1 mL
INACTIVE INGREDIENTS: Benzalkonium Chloride; Edetate Disodium; Glycerin; POLYETHYLENE GLYCOL, UNSPECIFIED; POVIDONE, UNSPECIFIED; Propylene Glycol; Sodium Phosphate, Dibasic, Anhydrous; Sodium Phosphate, Monobasic, Anhydrous; Water

Breaze®
Nasal Spray Moisturizing

DRUG FACT

ACTIVE INGREDIENT

Oxymetazoline hydrochloride, 0.05%

PURPOSE

Nasal Decongestant

Uses

♦ Temporarily relieves nasal congestion due to:
♦ Common cold. Hay fever. Sinusitis
♦ Upper respiratory allergies
♦ Shrinks swollen nasal membranes so you can breathe more freely

Warnings

Ask a doctor before use if you have

♦ High blood pressure
♦ Heart disease
♦ Diabetes
♦ Thyroid diseases
♦ Trouble urinating due to enlarged prostate gland

When using this product

Do not use more than directed

♦ Do not use for more than 3 days. Use only as directed. Frequent or prolonged use may cause nasal congestion to recur or worsen.
♦ Temporary discomfort such as burning, stinging, sneezing, or an increase in nasal discharge may occur
♦ Use of this container by more than one person may spread infection

Stop use and ask a doctor if symptoms persist

PREGNANCY OR BREAST FEEDING

If pregnant or breast- feeding, ask a health professional before use.

Keep out of reach of children. If swallowed, get medical help or contact a Poison Control Center right away.

Directions

Adult & children 6 to under 12 years of age (with adult supervision): 2 to 3 sprays in age nostril not more often than every 10 to 12 hours. Do not exceed 2 doses in any 24 –hr period.

Children under 6 years of age: ask a doctor. To spray, squeeze bottle quickly and firmly. Do not tilt head backward while spraying. Wipe nozzle clean after use.

Other information

♦ Store between 20C to 25C (68 to 77F).
♦ Retain carton for future reference on full labeling.

Inactive Ingredients

Benzalkonium Chloride, Edetate Disodium, Glycerin, Polyethelene Glycol, Povidone, Propylene Glycol, Sodium Diphospahte Dibasic, Sodium Phosphate Monobasic, Water.

Question or Comments?

1-888-995-9935

Manufactured by:
Samson Pharmaceutical
Commerce, CA 90040
Made in USA

Visit our website at
www.samson.pharmaceutical.com
Made in USA

PRINCIPAL DISPLAY PANEL - 30 mL Bottle Carton

MADE IN THE U.S.A.
WITH PRIDE

Breaze®

Relieves Congestion

Nasal
Spray

Moisturizing

12 Hour Relief

- Oxymetazoline HCl
  Nasal Solution
- Nasal Decongestant

1 FL OZ (30 mL)